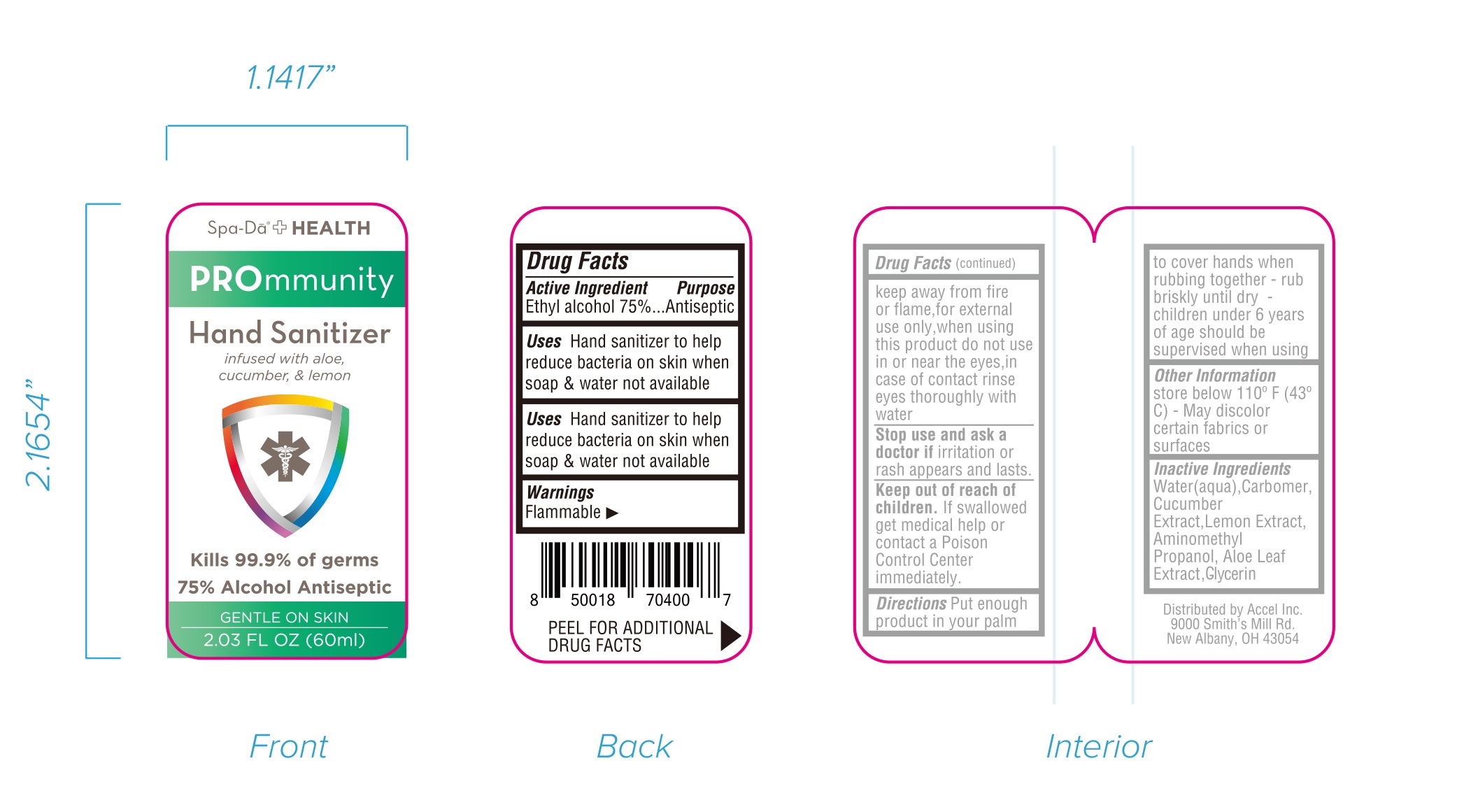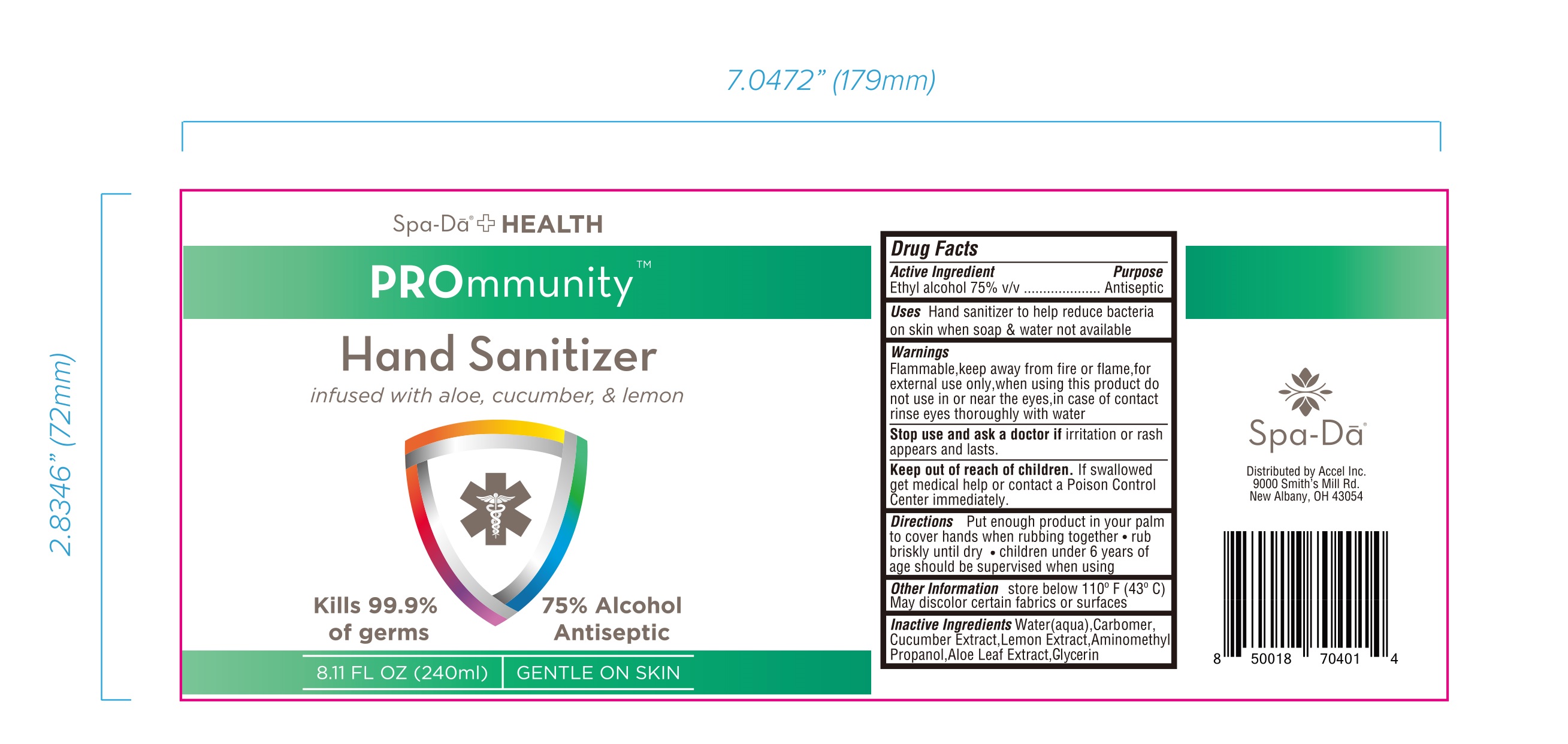 DRUG LABEL: Hand Sanitizer
NDC: 52807-022 | Form: LIQUID
Manufacturer: Guangdong Longtai Industry Co.,LTD
Category: otc | Type: HUMAN OTC DRUG LABEL
Date: 20201120

ACTIVE INGREDIENTS: ALCOHOL 75 mL/100 mL
INACTIVE INGREDIENTS: CUCUMBER; WATER; CARBOMER HOMOPOLYMER, UNSPECIFIED TYPE; LEMON; AMINOMETHYLPROPANOL; GLYCERIN; ALOE VERA LEAF

52807-022
Hand Sanitizer

Active Ingredient

Ethyl alcohol 75% v/v

Purpose

Antiseptic

INDICATIONS AND USAGE

Hand sanitizer to help reduce bacteria on skin when soap & water not available

Warnings

Flammable,keep away from fire or flame.for external use only.

Do not use

/

when using this product do not use in or near the eyes.in case of contact rinse eyes thoroughly with water

Stop use and ask a doctor if irritation or rash appears and lasts.

KEEP OUT OF REACH OF CHILDREN

Keep out of reach ol children. If swallowed get medical help or contact a Poison Control Center immediately.

DOSAGE AND ADMINISTRATION

Put enoug1h product i1n your palm to cover hands when rubbing together
rub briskly until dry
children under 6 years of age should be supervised when using

Other information

store below 110°F (43°C)
May discolor certain fabrics or surfaces

INACTIVE INGREDIENT

Water(aqua), Carbomer, Ctucumber Extract,Lemon Extract,Aminomethyl Propanol,A.loe Leaf Extract,Glyoerin